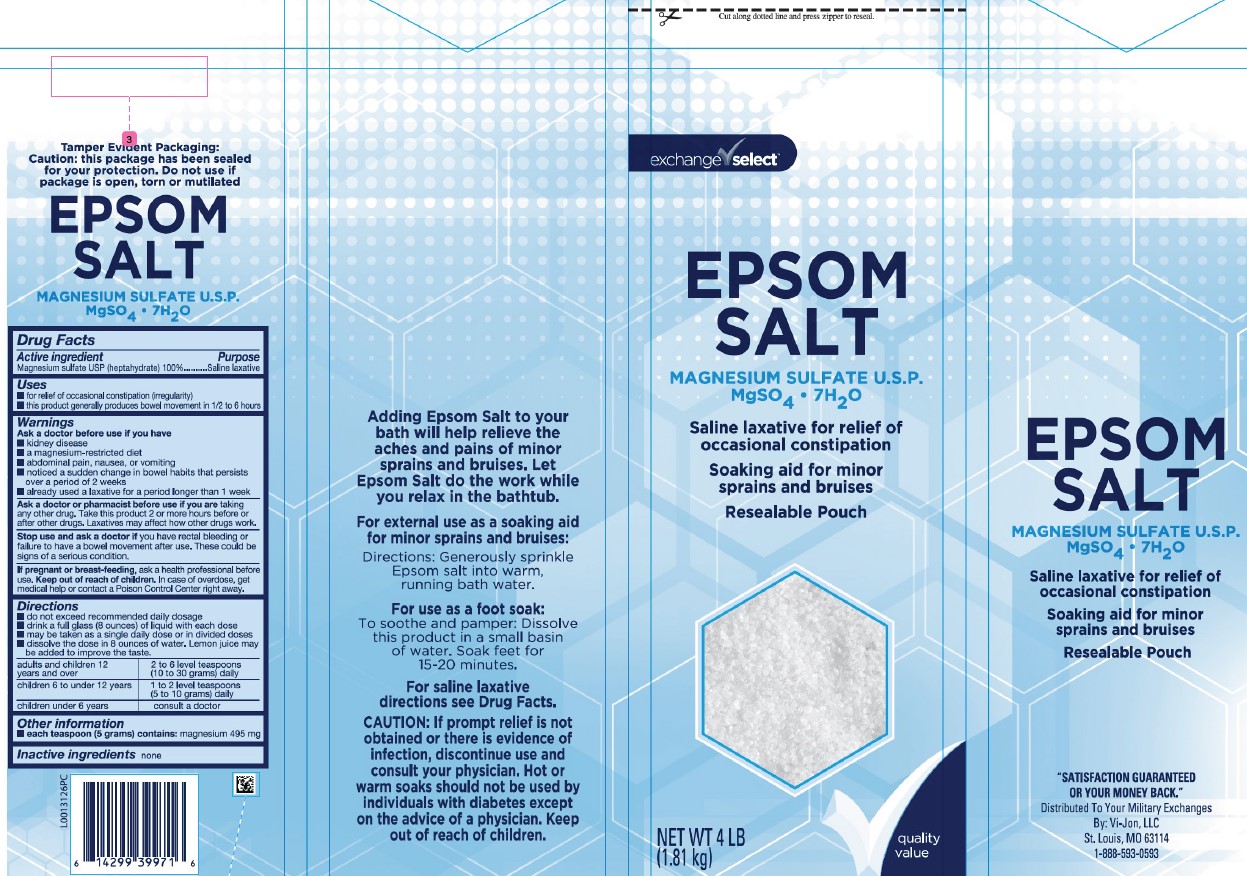 DRUG LABEL: Epsom Salt
NDC: 55301-602 | Form: GRANULE, FOR SOLUTION
Manufacturer: Your Military Exchanges
Category: otc | Type: HUMAN OTC DRUG LABEL
Date: 20260212

ACTIVE INGREDIENTS: MAGNESIUM SULFATE HEPTAHYDRATE 1 g/1 g

Exchange Select 602.002/602AA
Epsom Salt

Tamper Evident Statement

Tamper Evident Packaging:

Caution: this package has been sealed for your protection. Do not use if package is open, torn or mutilated.

EPSOM SALT

MAGNESIUM SULFATE U.S.P.

MgSO4 • 7H2O

Active ingredient

Magnesium sulfate USP (Heptahydrate) 100%

Purpose

Saline laxative

Uses

- for relief of occasional constipation (irregularity)
- this product generally produces bowel movement in 1/2 to 6 hours

Warnings

for this product

Ask a doctor before use

- kidney disease
- a magnesium-restricted diet
- abdominal pain, nausea or vomiting
- noticed a sudden change in bowel habits that persists over a period of 2 weeks
- already used a laxative for a period longer than 1 week.

Ask a doctor or pharmacist before use if you are

taking any other drug. Take this product 2 or more hours before or after other drugs. Laxatives may affect how other drugs work.

Stop use and ask a doctor if

you have rectal bleeding or failure to have a bowel movement after use. These could be signs of a serious condition.

If pregnant or breast-feeding,

ask a health professional before use.

Keep out of reach of children.

In case of overdose, get medical help or contact a Poison Control Center right away.

Directions

- do not exceed recommended daily dosage
- drink a full glass (8 ounces) of liquie with each dose
- may be taken as a single daily dose or in divided doses
- dissolve the dose in 8 ounces of water. Lemon juice may be added to improve the taste

adults and children 12 years and over - 2 to 6 level teaspoons (10 to 30 grams) daily

children 6 to under 12 years - 1 to 2 level teaspoons (5 to 10 grams) daily

children under 6 years - consult a doctor

Other information

- each teaspoon (5 grams) contains: magnesium 495 mg

Inactive Ingredient

None

Side panels

Adding Epsom Salt to your bath will help relieve the aches and pains of minor sprains and bruises. Let Epsom Salt do the work while your relax in the bathtub.

For external use as a soaking aid for minor sprains and bruises:

Directions: Generously sprinkle Epsom salt into warm, running bath water.

For use as a foot soak:

To soothe and pamper: Dissolve this product in a small basin of water. Soak feet for 15-20 minutes.

For saline laxative directions see Drug Facts.

CAUTION: If prompt relief is not obtained or there is evidence of infection, discontinue use and consult your physician. Hot or warm soaks should not be used by individuals with diabetes except on the advice of a physician. Keep out of reach of children.

EPSOM SALT
MAGNESIUM SULFATE U.S.P.
MgSO4 • 7H2O

Saline laxative for relief of occasional constipation

Soaking aid for minor sprains and bruises

Resealable Pouch

ADVERSE REACTION

"SATISFACTION GUARANTEED OR YOUR MONEY BACK."

Distributed To Your Military Exchanges

By: Vi-Jon, LLC

St. Louis, MO 63114

1-888-593-0593

principal display panel

Cut along dotted line and press zipper to reseal.

exchange select™

EPSOM SALT

MAGNESIUM SULFATE U.S.P.

MgSO4 7H2O

Saline laxative for relief of occasional constipation

Soaking aid for minor sprains and bruises

Resealable Pouch

quality value

NET WT 4 LB (1.81 kg)